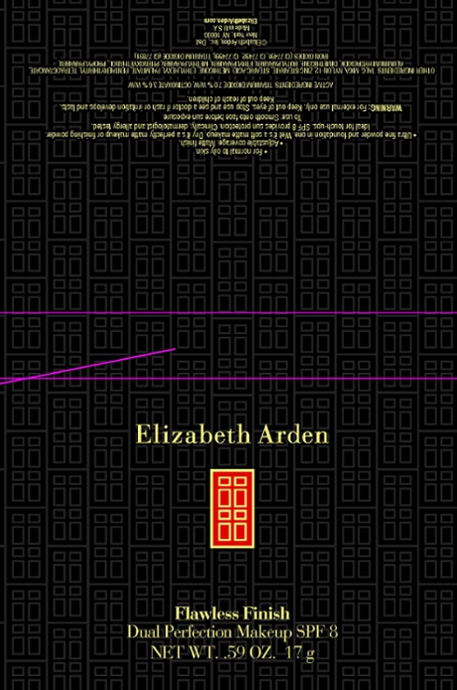 DRUG LABEL: Flawless Finish Dual Perfection Makeup SPF 8 Mocha
NDC: 67938-1165 | Form: POWDER
Manufacturer: Elizabeth Arden, Inc
Category: otc | Type: HUMAN OTC DRUG LABEL
Date: 20110113

ACTIVE INGREDIENTS: TITANIUM DIOXIDE 1.19 g/17 g; OCTINOXATE 0.59 g/17 g
INACTIVE INGREDIENTS: TALC; MICA; OCTINOXATE; ZINC STEARATE; STEARIC ACID; DIMETHICONE; ETHYLHEXYL PALMITATE; ALUMINUM HYDROXIDE; PHENOXYETHANOL; METHYLPARABEN; BUTYLPARABEN; ETHYLPARABEN; PROPYLPARABEN

BP1165

DESCRIPTION

For normal to oily skin. Adjustable coverage. Matte finish. Ultra fine powder and foundation in one. Wet it's a soft matte makeup. Dry it's a perfectly matte makeup or finishing powder. Ideal for touch-ups. SPF 8 provides sun protection. Clinically, dermatologist, and allergy tested.

INDICATIONS AND USAGE

To Use: Smooth on to face before sun exposure.

WARNINGS

Warning: For external use only. Keep out of eyes. Stop use and see a doctor is rash or irritation develops and lasts. Keep out of reach of children.

OTC - ACTIVE INGREDIENT

Active Ingredients: Titanium Dioxide 7.0% w/w, Octinoxate 3.6% w/w.

INACTIVE INGREDIENT

Other Ingredients: Talc, Zinc Stearate, Nylon-12, Dimethicone, Ethylhexyl Palmitate, Pentaerythrityl Tetraethylhexanoate, Methicone, Aluminum Hydroxide, Butylparaben, Ethylparaben, Isobutylparaben, Methylparaben, Phenoxyethanol, Propylparaben, Iron Oxides, Mica, Titanium Dioxide.

DOSAGE & ADMINISTRATION

Smooth on to face.

OTC - KEEP OUT OF REACH OF CHILDREN

Keep out of reach of children.

OTC - PURPOSE

SPF 8 provides sun protection.

OTC - WHEN USING

Keep out of eyes.